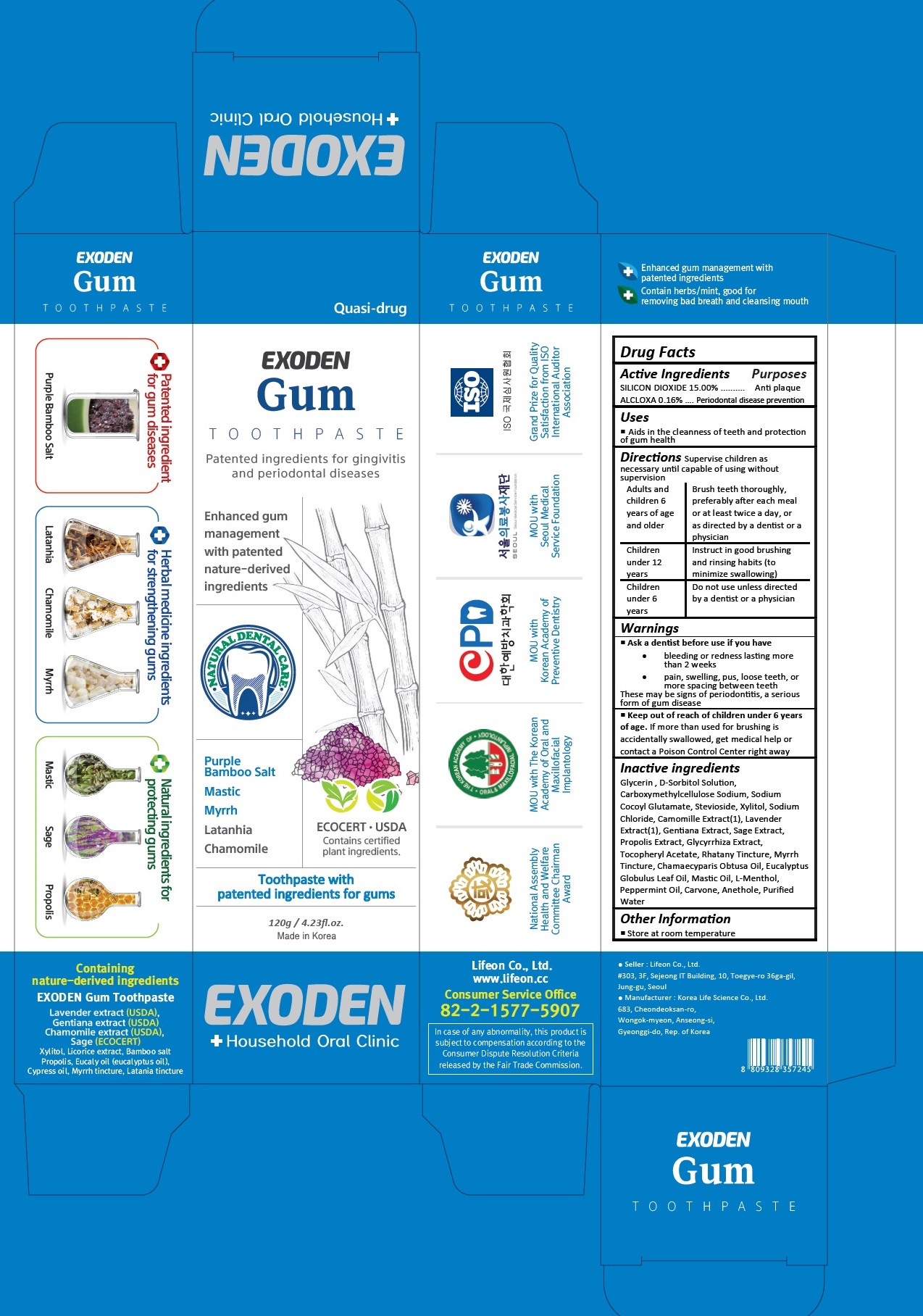 DRUG LABEL: Exoden Gum
NDC: 70602-007 | Form: PASTE
Manufacturer: LIFEON Corp.
Category: otc | Type: HUMAN OTC DRUG LABEL
Date: 20210312

ACTIVE INGREDIENTS: ALCLOXA 0.16 g/100 g; SILICON DIOXIDE 15 g/100 g
INACTIVE INGREDIENTS: GLYCERIN; SORBITOL SOLUTION; CARBOXYMETHYLCELLULOSE SODIUM, UNSPECIFIED; SODIUM COCOYL GLUTAMATE; XYLITOL; GLUCOSYL STEVIOL; CHAMOMILE; SODIUM CHLORIDE; LAVANDULA ANGUSTIFOLIA SUBSP. ANGUSTIFOLIA FLOWER; CLARY SAGE; GENTIANA LUTEA ROOT; PROPOLIS WAX; LICORICE; .ALPHA.-TOCOPHEROL ACETATE; CHAMAECYPARIS OBTUSA WOOD OIL; EUCALYPTUS OIL; LEVOMENTHOL; PEPPERMINT OIL; CARVONE, (+/-)-; ANETHOLE; WATER

70602-007_Exoden Gum Toothpaste

ACTIVE INGREDIENT

Silicon dioxide 15%

Aluminum Chlorohydroxy Allantoinate 0.16%

PURPOSE

Anti plaque

Periodontal disease prevention

INDICATIONS AND USAGE

Aids in cleanness of teeth and protection of gum health

DOSAGE AND ADMINISTRATION

Supervise children as necessary until capable of using without supervision

Adults and children 6 years of age and older: Brush teeth thoroughly, preferably after each meal or at least twice a day, or as directed by a dentist or a physician

Children under 12 years: Instruct in good brushing and rinsing habits (to minimize swallowing)

Children under 6 years: Do not use unless directed by a dentist or a physician

WARNINGS

Ask a dentist before use if you have
• bleeding or redness lasting more than 2 weeks
• pain, swelling, pus, loose teeth, or more spacing between teeth
These may be signs of periodontitis, a serious form of gum disease

Keep out of reach of children under 6 years of age. If more than used for brushing is accidentally swallowed, get medical help or contact a Poison Control Center right away

INACTIVE INGREDIENT

Glycerin , D-Sorbitol Solution, Carboxymethylcellulose Sodium, Sodium Cocoyl Glutamate, Stevioside, Xylitol, Sodium Chloride, Camomille Extract(1), Lavender Extract(1), Gentiana Extract, Sage Extract, Propolis Extract, Glycyrrhiza Extract, Tocopheryl Acetate, Rhatany Tincture, Myrrh Tincture, Chamaecyparis Obtusa Oil, Eucalyptus Globulus Leaf Oil, Mastic Oil, L-Menthol, Peppermint Oil, Carvone, Anethole, Purified Water